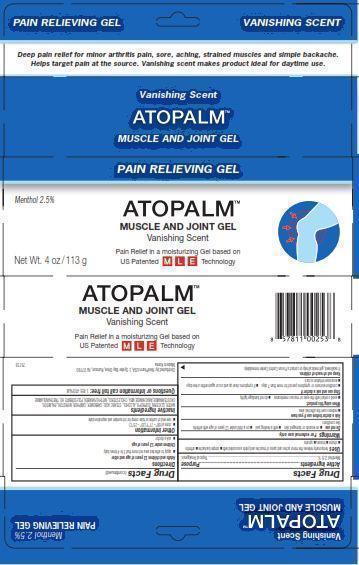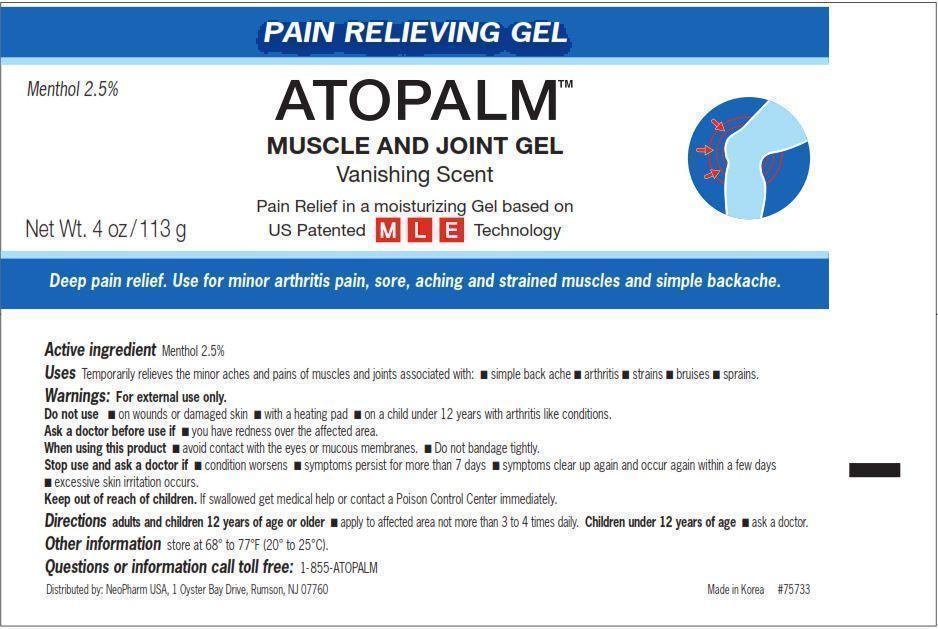 DRUG LABEL: ATOPALM MUSCLE AND JOINT
NDC: 51141-0240 | Form: GEL
Manufacturer: NeoPharm Co., Ltd.
Category: otc | Type: HUMAN OTC DRUG LABEL
Date: 20120815

ACTIVE INGREDIENTS: MENTHOL 2.5 g/100 g
INACTIVE INGREDIENTS: WATER; GLYCERIN; ISOPROPYL ALCOHOL; STEARIC ACID; MYRISTOYL/PALMITOYL OXOSTEARAMIDE/ARACHAMIDE MEA; STEARIC ACID; CHOLESTEROL; METHYLPARABEN; POLYSORBATE 60; TROLAMINE

ATOPALM MUSCLE AND JOINT GEL

Drug Facts

Active Ingredients

Menthol 2.5%

Purpose

Topical Analgesic

INDICATIONS AND USAGE

Uses temporarily relieves the minor aches and pains of muscles and joints associated with:

- simple backache
- arthritis
- strains
- bruises
- sprains

Warnings For external use only.

Do not use

- on wounds or damaged skin
- with a heating pad
- on a child under 12 years of age with arthritis like conditions

Ask a doctor before use if you have redness over the affected area.

When using this product

- avoid contact with eyes or mucous membranes
- do not bandage tightly

Stop use and ask a doctor if

- condition worsens or symptoms persist for more than 7 days
- symptoms clear up and occur again within a few days
- excessive skin irritation occurs

Keep out of reach of children. If swallowed, get medical help or contact a Poison Control Center immediately.

Directions

adults and children 12 years of age or older
apply to affected area not more that 3 to 4 times daily

children under 12 years of age
ask a doctor

Other Information

- store at 68 - 77 degree Fahrenheit (20 - 25 degrees Celsius)
- see end of carton or tube crimp for lot number and expiration date

Inactive Ingredients

WATER, GLYCERIN, ISOPROPYL ALCOHOL, STEARIC ACID, CARBOMER, CAMPHOR, MYRISTOYL/PALMITOYL OXOSTEARAMIDE/ARACHAMIDE MEA, CHOLESTEROL, METHYLPARABEN, POLYSORBATE 60, TRIETHANOLAMINE

Questions? Call 1-855-ATOPALM

Distributed by: NeoPharm Co., 1 Oyster Bay Drive, Rumson, NJ 07760

Made in Korea

PACKAGE LABEL

Pain Relieving Gel VANISHING SCENT
Deep pain relief for minor arthritis pain, sore, aching, strained muscles and simple backache.
Helps target pain at the source. Vanishing scent makes product ideal for daytime use.
Vanishing Scent
ATOPALM (TM)
MUSCLE AND JOINT GEL
Menthol 2.5%
Pain Relief in moisturizing Gel based on US Patented MLE Technology
Net Wt. 4 oz/113 g